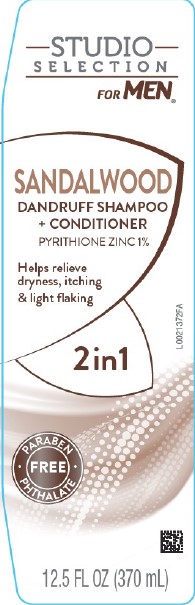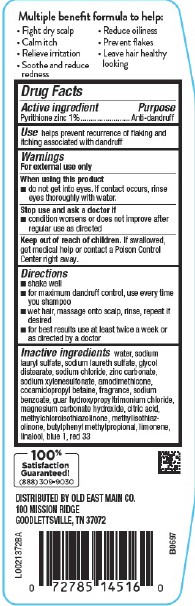 DRUG LABEL: 2 in 1 Dandruff
NDC: 55910-921 | Form: SHAMPOO
Manufacturer: Old East Main Co.
Category: otc | Type: HUMAN OTC DRUG LABEL
Date: 20251223

ACTIVE INGREDIENTS: PYRITHIONE ZINC 10 mg/1 mL
INACTIVE INGREDIENTS: WATER; SODIUM LAURYL SULFATE; SODIUM LAURETH SULFATE; GLYCOL DISTEARATE; SODIUM CHLORIDE; ZINC CARBONATE; SODIUM XYLENESULFONATE; AMODIMETHICONE (800 CST); COCAMIDOPROPYL BETAINE; SODIUM BENZOATE; GUAR HYDROXYPROPYLTRIMONIUM CHLORIDE (1.7 SUBSTITUENTS PER SACCHARIDE); MAGNESIUM CARBONATE HYDROXIDE; CITRIC ACID MONOHYDRATE; METHYLCHLOROISOTHIAZOLINONE; METHYLISOTHIAZOLINONE; BUTYLPHENYL METHYLPROPIONAL; LIMONENE, (+)-; LINALOOL, (+/-)-; FD&C BLUE NO. 1; D&C RED NO. 33

Studio Selection D57.000/D57AA-AB
Sandalwood 2-in-1 Dandruff Shampoo + Conditioner

Claims

Multiple benefit formula to help:

- Fight dry scalp
- Calm itch
- Relieve irritation
- Soothe and reduce redness
- Reduce oiliness
- Prevent flakes
- Leave hair healthy looking

Active Ingredient

Pyrithione zinc 1%

Purpose

Anti-dandruff

Use

helps prevent recurrence of flaking and itching associated with dandruff

Warnings

For external use only

When using this product

- do not get into eyes. If contact occurs, rinse eyes thoroughly with water.

Stop use and ask a doctor if

- condition worsens or does not improve after regular use as directed

Keep out of reach of children.

If swallowed, get medical help or contact a Poison Control Center right away.

Directions

- shake well
- for maximum dandruff control, use every time you shampoo
- wet hair, massage onto scalp, rinse, repeat if desired
- for best results use at least twice a week or as directed by a doctor

Inactive ingredients

water, sodium lauryl sulfate, sodium laureth sulfate, glycol distearate, sodium chloride, zinc carbonate, sodium xylenesulfonate, amodimethicone, cocamidopropyl betaine, fragrance, sodium benzoate, guar hydroxypropyltrimonium chloride, magnesium carbonate hydroxide, citric acid, methylchloroisothiazolinone, methylisothiazolinone, butylphenyl methylpropional, limonene, linalool, blue 1, red 33

Adverse Reaction

100% Satisfaction Guaranteed!

(888) 309-9030

DISTRIBUTED BY OLD EAST MAIN CO.

100 MISSION RIDGE

GOODLETTSVILLE, TN 37072

Principal Panel Display

STUDIO SELECTION

FOR MEN®

SANDALWOOD

DANDRUFF SHAMPOO

+ CONDITIONER

PYRITHIONE ZINC 1%

Helps relieve dryness, itching & light flaking

2in1

Paraben Phthalate Free

12.5 FL OZ (370 mL)